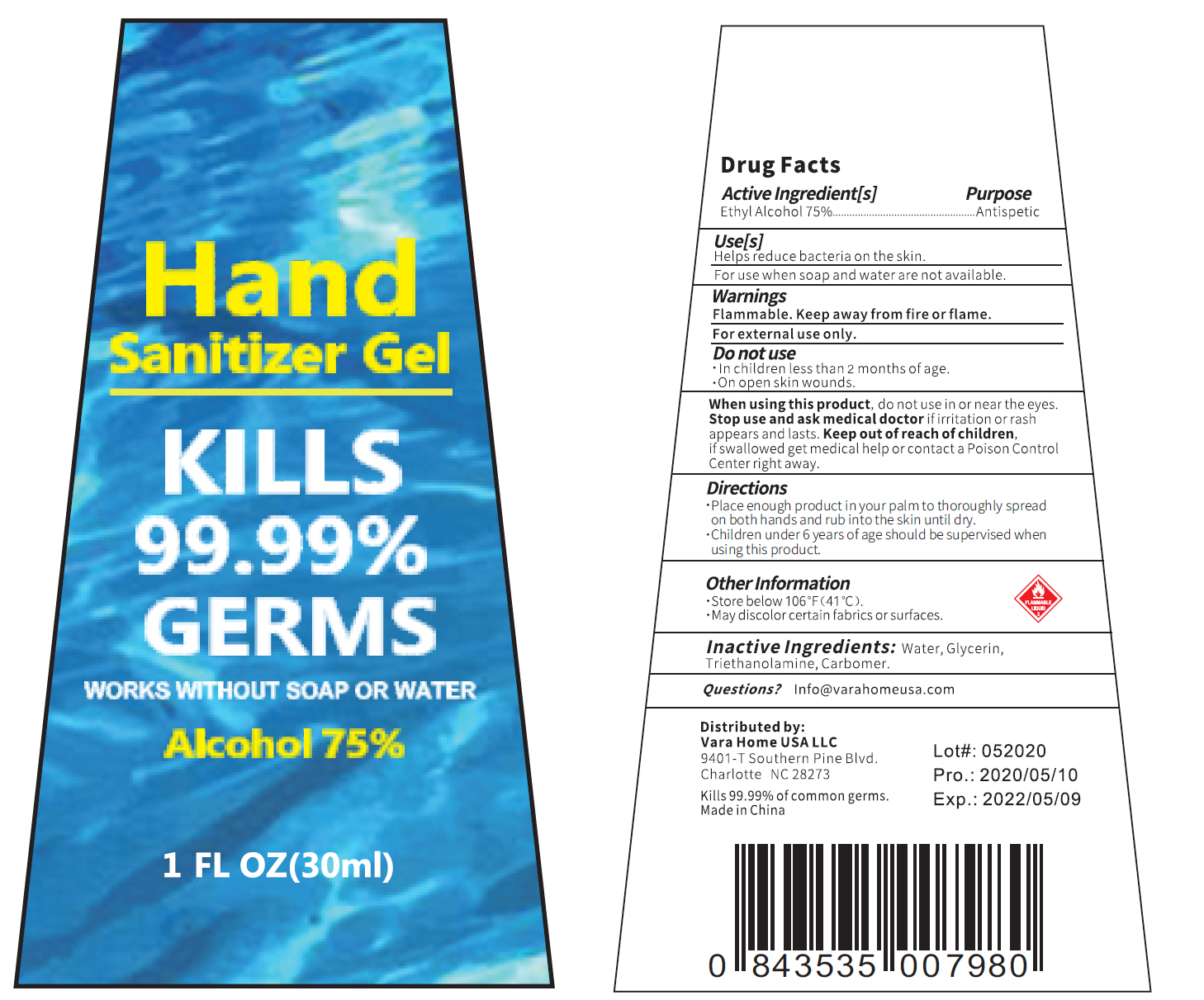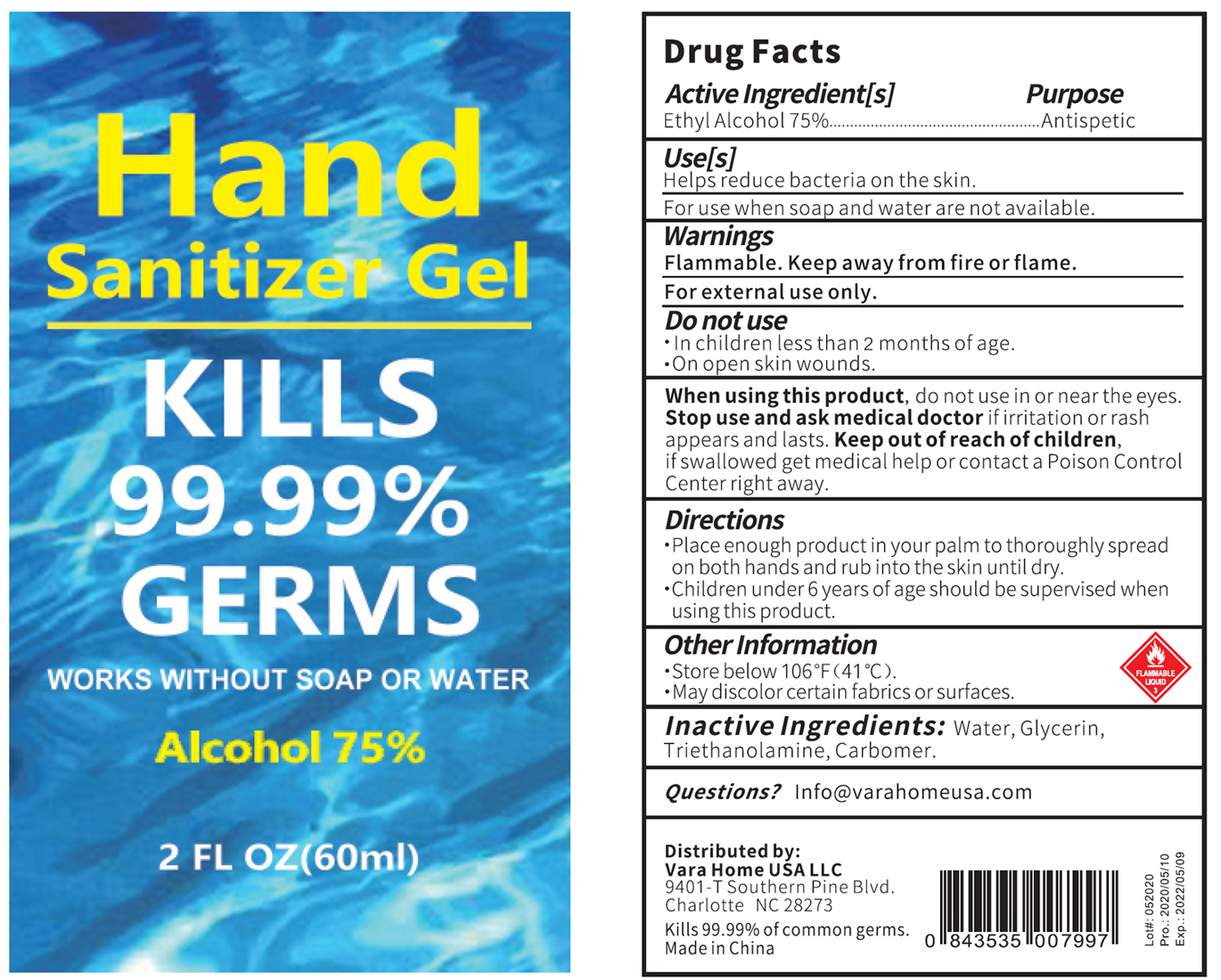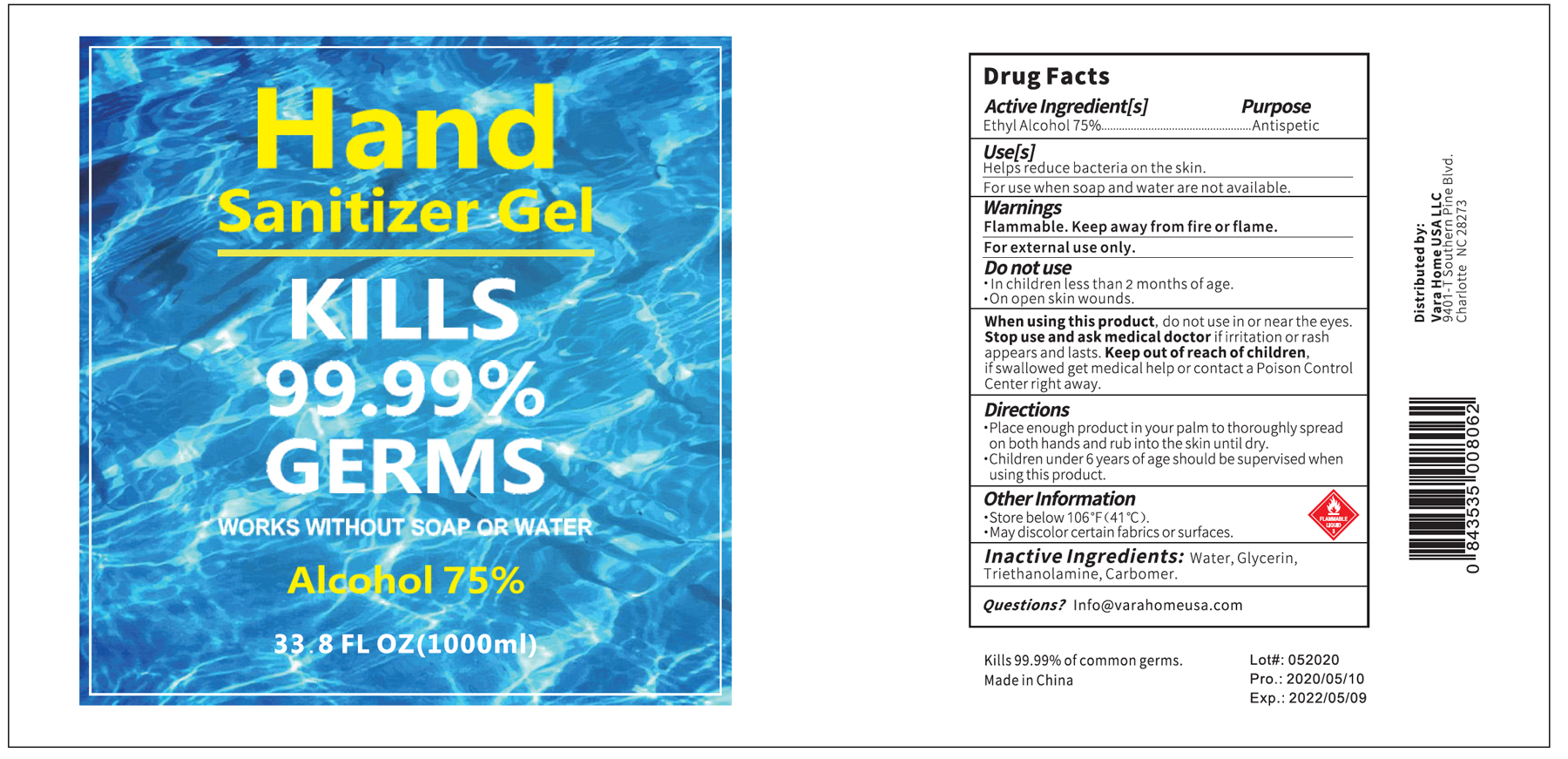 DRUG LABEL: Hand Sanitizer
NDC: 79060-002 | Form: GEL
Manufacturer: Vara Home Usa Llc
Category: otc | Type: HUMAN OTC DRUG LABEL
Date: 20200612

ACTIVE INGREDIENTS: ALCOHOL 75 mL/100 mL
INACTIVE INGREDIENTS: CARBOMER HOMOPOLYMER, UNSPECIFIED TYPE; GLYCERIN; TROLAMINE; WATER

Hand Sanitizer Gel

Active Ingredient(s)

Alcohol 75% v/v. Purpose: Antiseptic

Purpose

Antiseptic, Hand Sanitizer

Use

Hand Sanitizer to help reduce bacteria that potentially can cause disease. For use when soap and water are not available.

Warnings

Flammable. Keep away from heat or flame.

For external use only.

Do not use

- in children less than 2 months of age
- on open skin wounds

When using this product

do not use in or near the eyes.

Stop use and ask medical doctor

if irritation or rash appears and lasts.

Keep out of reach of children. If swallowed, get medical help or contact a Poison Control Center right away.

Directions

- Place enough product in your palm to thoroughly spread on both hands and rub into the skin until dry.
- Children under 6 years of age should be supervised when using this product.

Other information

- Store below 106F (41F).
- May discolor certain fabrics or surfaces.

Inactive ingredients

Water, Glycerin, Triethanolamine, Carbomer

Package Label - Principal Display Panel

30 mL NDC: 79060-002-01

60 mL NDC:79060-002-02

1000 mL NDC: 79060-002-03